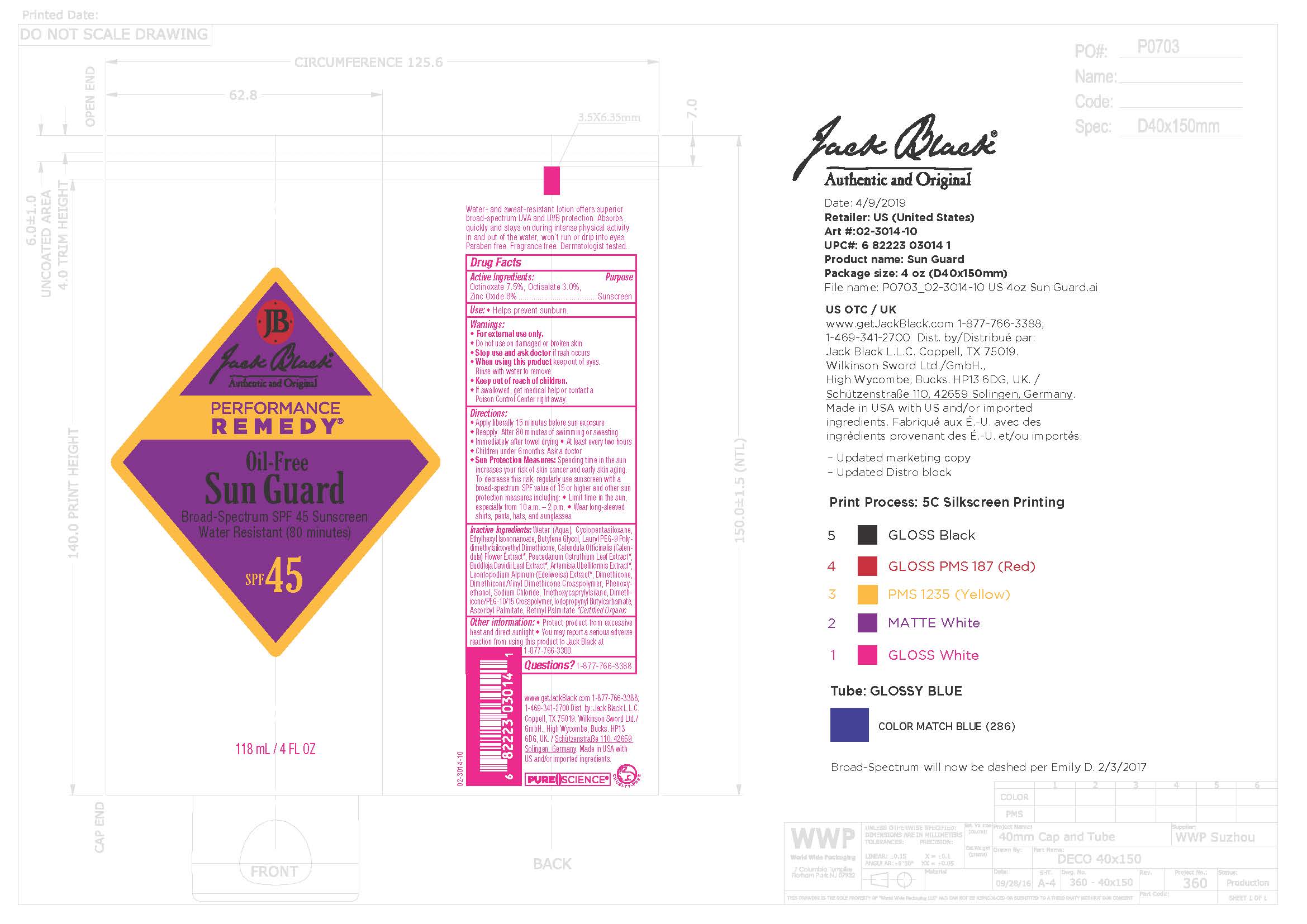 DRUG LABEL: Jack Black Sun Guard Sunscreen SPF45
NDC: 66738-304 | Form: LOTION
Manufacturer: Jack Black, LLC
Category: otc | Type: HUMAN OTC DRUG LABEL
Date: 20231108

ACTIVE INGREDIENTS: OCTISALATE 3 g/1000 g; OCTINOXATE 7.5 g/1000 g; ZINC OXIDE 8 g/1000 g
INACTIVE INGREDIENTS: BUTYLENE GLYCOL; PHENOXYETHANOL; IODOPROPYNYL BUTYLCARBAMATE; WATER; SODIUM CHLORIDE; VITAMIN A PALMITATE; ASCORBYL PALMITATE; CALENDULA OFFICINALIS FLOWER; LEONTOPODIUM ALPINUM FLOWER; PEUCEDANUM OSTRUTHIUM LEAF; BUDDLEJA DAVIDII LEAF; ARTEMISIA UMBELLIFORMIS FLOWER; CYCLOMETHICONE 5; DIMETHICONE; DIMETHICONE/VINYL DIMETHICONE CROSSPOLYMER (SOFT PARTICLE); LAURYL PEG-9 POLYDIMETHYLSILOXYETHYL DIMETHICONE; ETHYLHEXYL ISONONANOATE; TRIETHOXYCAPRYLYLSILANE; GLYCERIN

Jack Black Sun Guard Sunscreen SPF45 Oil-Free, Water Resistant (80 min)

Active Ingredients

Octisalate 3.0% Sunscreen

Octinoxate 7.5% Sunscreen

Zinc Oxide 8.0% Sunscreen

Uses

Helps prevent sunburn

Uses

Helps prevent sunburn

Warnings

- For external use only
- Do not use on damaged or broken skin
- Stop use and ask doctor if rash occurs
- When using this product keep out of eyes
- Rinse with water to remove
- Keep out of reach of children
- If swallowed, get medical help or contact Poison Control Cneter right away

Directions

- Apply liberally 15 minutes before sun exposure
- Reapply: after 80 minutes of swimming or sweating
- Immediately after towel drying
- At least every two hours
- Children under 6 months: ask a doctor
- Spending time in the sun increases your risk of skin cancer and early skin aging.
- To decrease this risk, regularly use sunscreen with a broad spectrum SFP value of 15 or higher
- Limit time in the sun, eespecially from 10 a.m. - 2 p.m.

Inactive Ingredients

Artemisia Umbelliformis Extract, Ascorbyl Palmitate, Buddleja Davidii Leaf Extract, Butylene Glycol, Calendula Officinalis Flower Extract, Cyclopentasiloxane, Dimethicone, Dimethicone/PEG-10/15 Crosspolymer, Dimethicone/Vinyl Dimethicone Crosspolymer, Ethylhexyl Isononanoate, Glycerin, Iodopropynyl Butylcarbamate, Lauryl PEG-9 Polymethylsiloxethyl Dimethicone, Leontopodium Aloinum (Edelweiss) Extract, Penoxyethanol, Peucedanum Ostruthium Leaf Extract, Retinyl Palmitate, Sodium Chloride, Triethoxycaprylylsilane, Water

KEEP OUT OF REACH OF CHILDREN

Other Information

- Protect product from exessive heat and direct sunlight.
- You may report a serious adverse reaction from using this product to Jack Black at 1-877-766-3388

Questions

1-877-766-3388

www.getjackblack.com